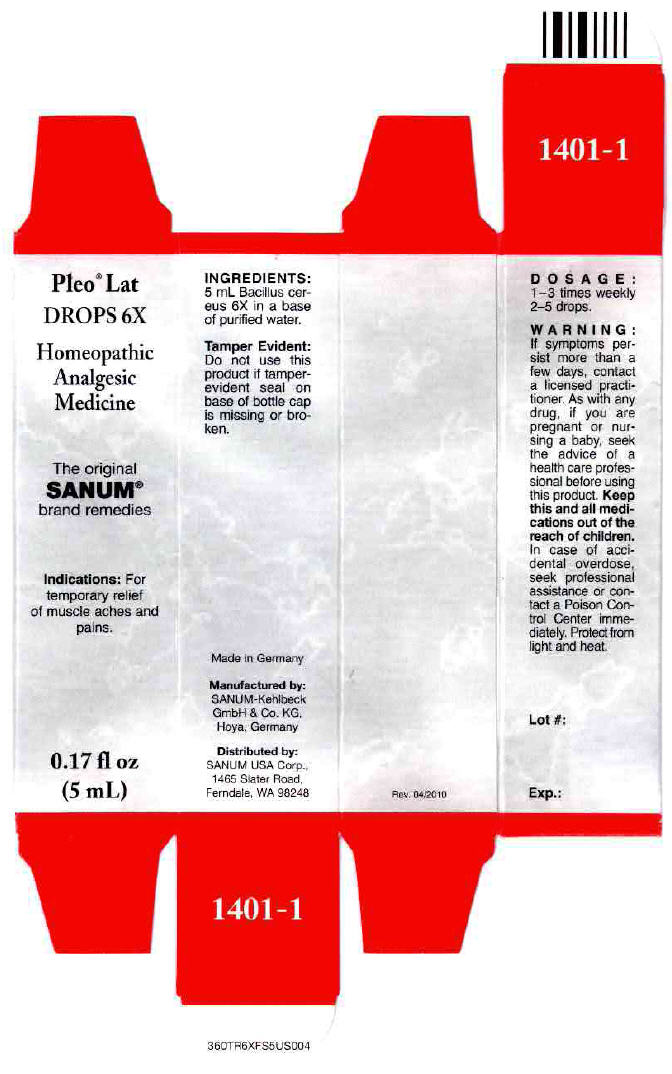 DRUG LABEL: Pleo Lat
NDC: 60681-1401 | Form: SOLUTION/ DROPS
Manufacturer: Sanum Kehlbeck GmbH & Co. KG
Category: homeopathic | Type: HUMAN OTC DRUG LABEL
Date: 20111111

ACTIVE INGREDIENTS: BACILLUS CEREUS 6 [hp_X]/5 mL
INACTIVE INGREDIENTS: water

Pleo® Lat
DROPS 6X

PURPOSE

Homeopathic Analgesic Medicine

Indications

For temporary relief of muscle aches and pains.

INGREDIENTS

INACTIVE INGREDIENT

5 mL Bacillus cereus 6X in a base of purified water.

Tamper Evident

Do not use this product if tamper-evident seal on base of bottle cap is missing or broken.

DOSAGE

1–3 times weekly 2–5 drops.

WARNING

If symptoms persist more than a few days, contact a licensed practitioner. As with any drug, if you are pregnant or nursing a baby, seek the advice of a health care professional before using this product.

KEEP OUT OF REACH OF CHILDREN

Keep this and all medications out of the reach of children. In case of accidental overdose, seek professional assistance or contact a Poison Control Center immediately.

STORAGE AND HANDLING

Protect from light and heat.

Made in Germany

Manufactured by:
SANUM-Kehlbeck
GmbH & Co. KG,
Hoya, Germany

Distributed by:
SANUM USA Corp.,
1465 Slater Road,
Ferndale, WA 98248

Rev. 04/2010

PRINCIPAL DISPLAY PANEL - 5 mL Bottle Carton

Pleo® Lat
DROPS 6X

Homeopathic
Analgesic
Medicine

The original
SANUM®
brand remedies

Indications: For
temporary relief
of muscle aches and
pains.

0.17 fl oz
(5 mL)